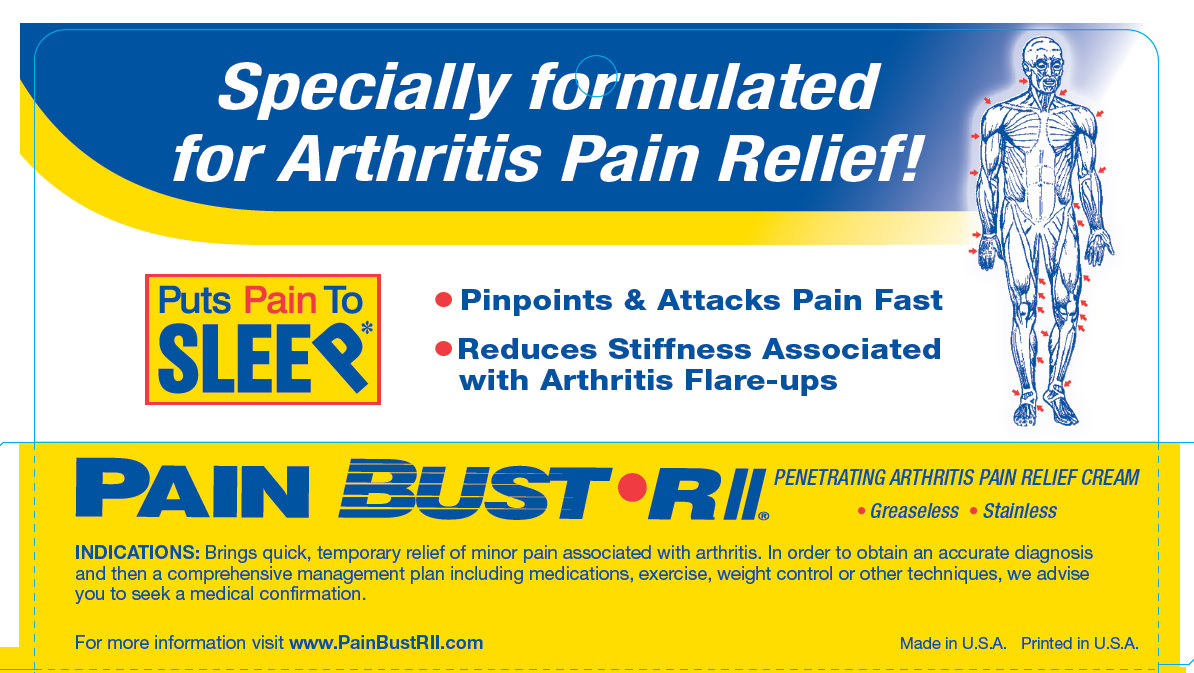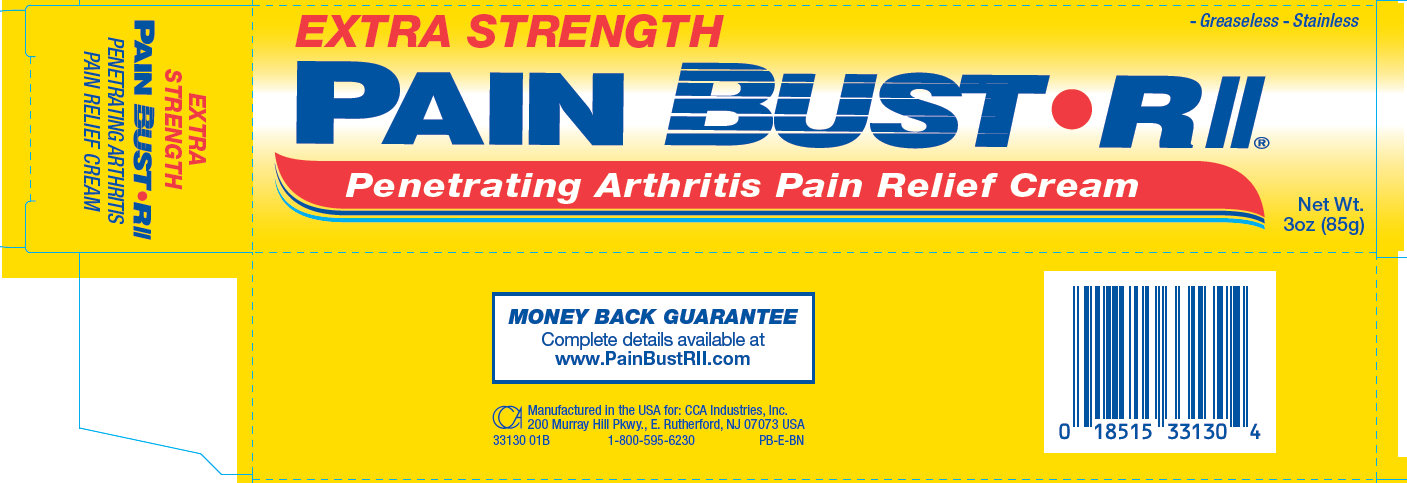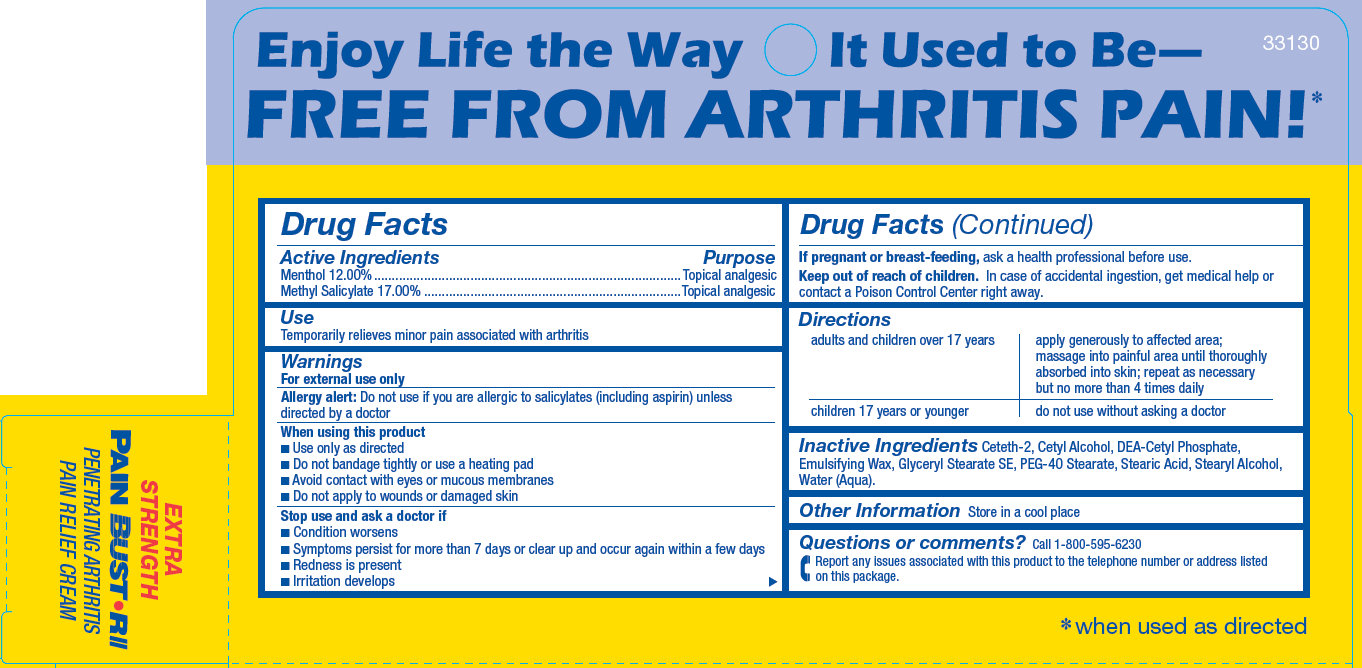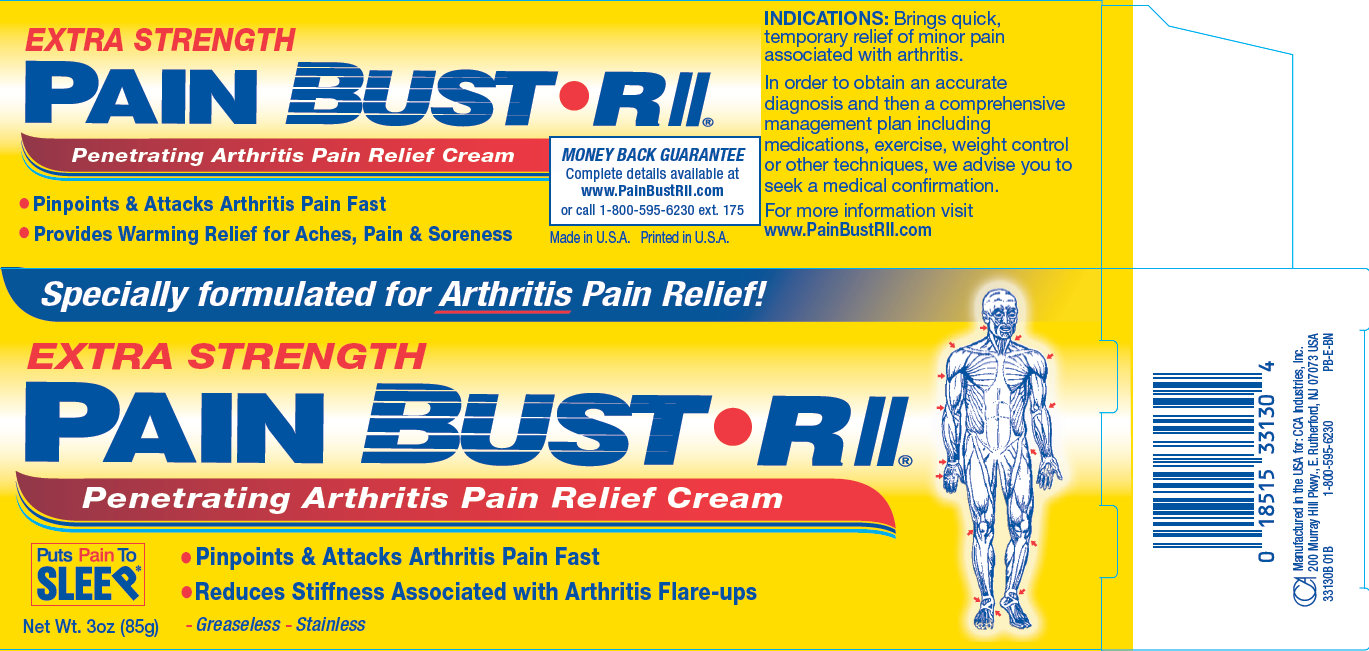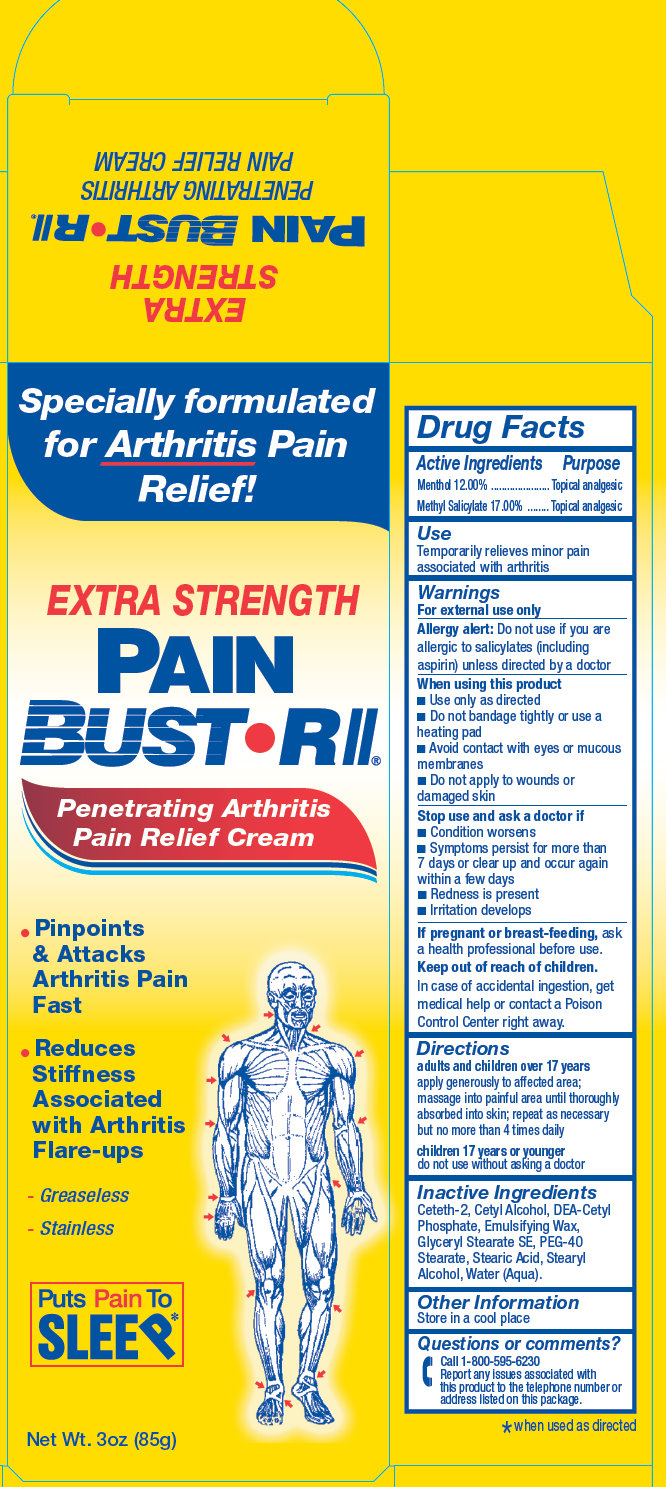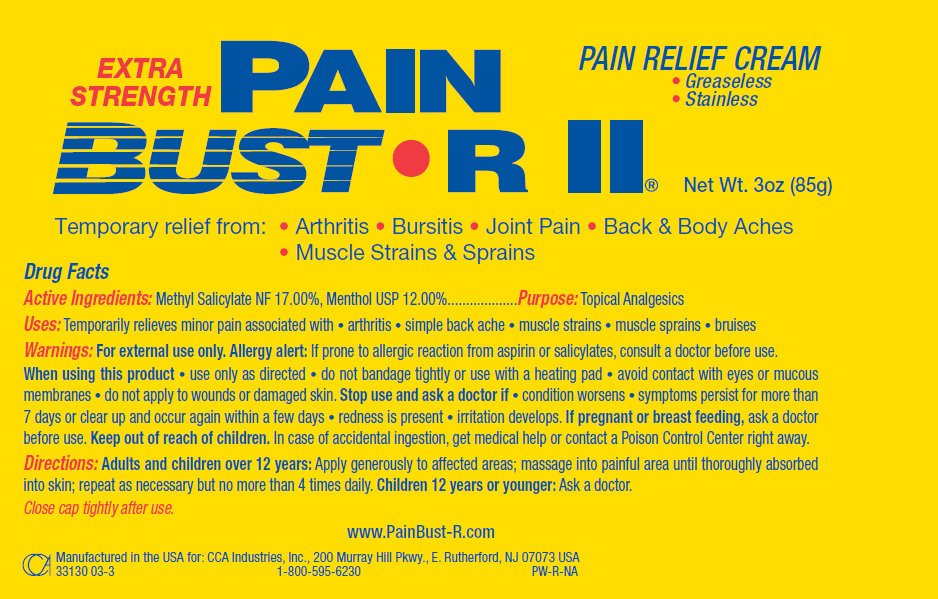 DRUG LABEL: PAIN BUST R II
NDC: 61543-3130 | Form: CREAM
Manufacturer: CCA Industries, Inc.
Category: otc | Type: HUMAN OTC DRUG LABEL
Date: 20190322

ACTIVE INGREDIENTS: MENTHOL 12 g/100 g; METHYL SALICYLATE 17 g/100 g
INACTIVE INGREDIENTS: CETETH-2; DIETHANOLAMINE CETYL PHOSPHATE; GLYCERYL MONOSTEARATE; PEG-40 STEARATE; STEARIC ACID; STEARYL ALCOHOL; WATER

PAIN BUST R II

Active Ingredients

Menthol 12.00%

Methyl Salicylate 17.00%

Purpose

Topical Analgesic

Use

Temporarily relieves minor pain associated with arthritis

Warnings

For external use only

Allergy alert: Do not use if you are allergic to salicylates (including aspirin) unless directed by a doctor.

When using this product

- Use only as directed
- Do not bandage tightly or use a heating pad
- Avoid contact with eyes or mucous membranes
- Do not apply to wounds or damaged skin

Stop use and ask a doctor if

- Condition worsens
- Symptoms persist for more than 7 days or clear up and occur again within a few days
- Redness is present
- Irritation develops

If pregnant or breast-feeding,

ask a health professional before use.

Keep out of reach of children

In case of accidental ingestion, get medical help or contact a Poison Control Center right away.

Directions

adults and children over 17 years | apply generously to affected area; massage into painful area until thoroughly absorbed into skin; repeat as necessary but no more than 4 times daily
children 17 years or younger | do not use without asking a doctor

Inactive Ingredients

Ceteth-2, Cetyl Alcohol, DEA-Cetyl Phosphate, Emulsifying Wax, Glyceryl Stearate SE, PEG-40 Stearate, Stearic Acid, Stearyl Alcohol, Water (Aqua).

Other Information

Store in a cool palce

Questions or comments?

Call 1-800-595-6230

Report any issues associated with this product to the telephone number or address listed on this package.